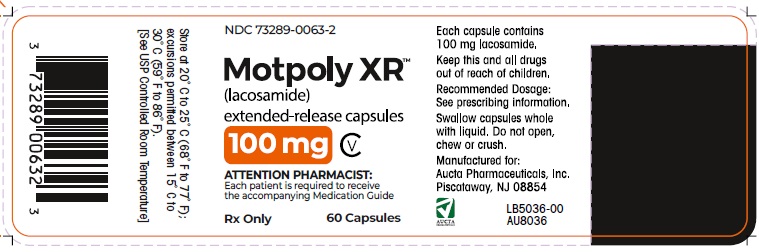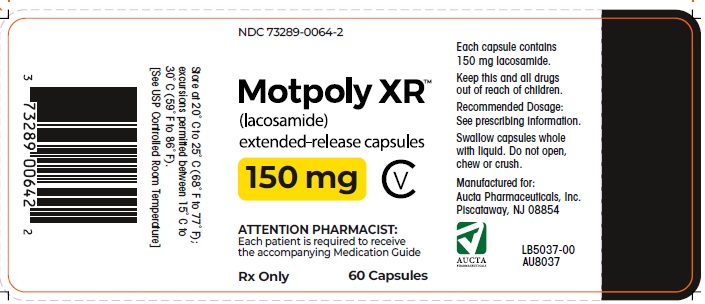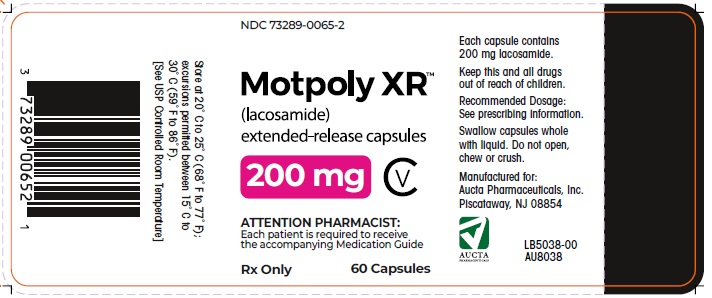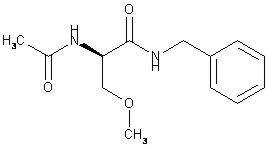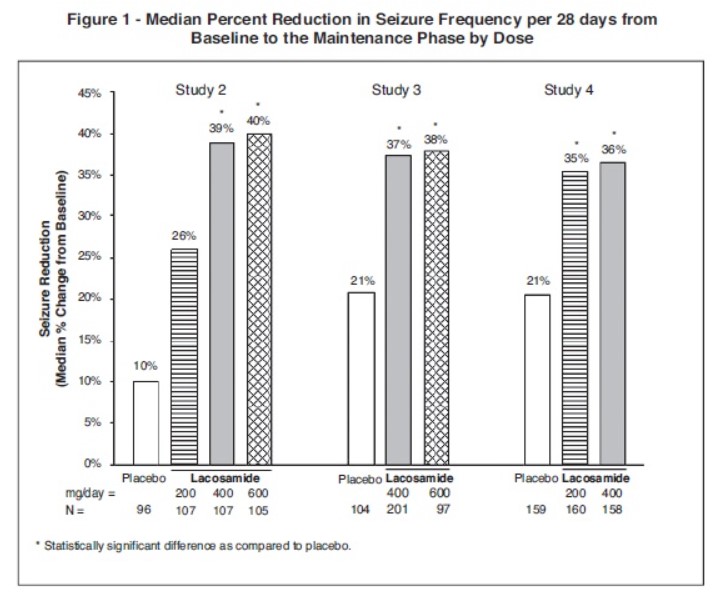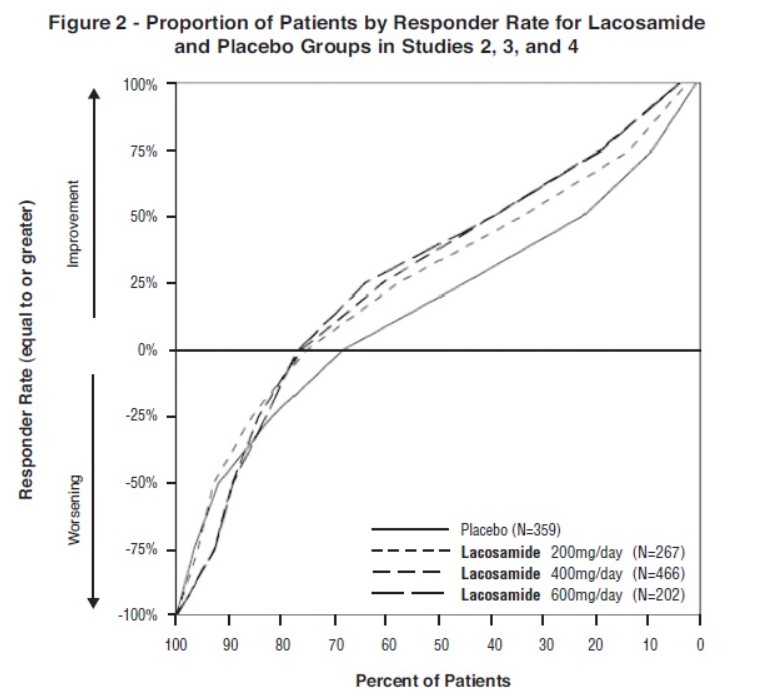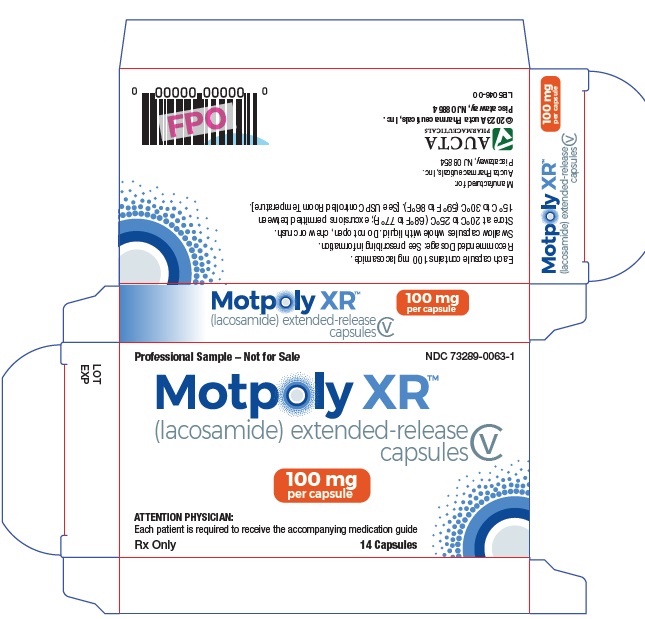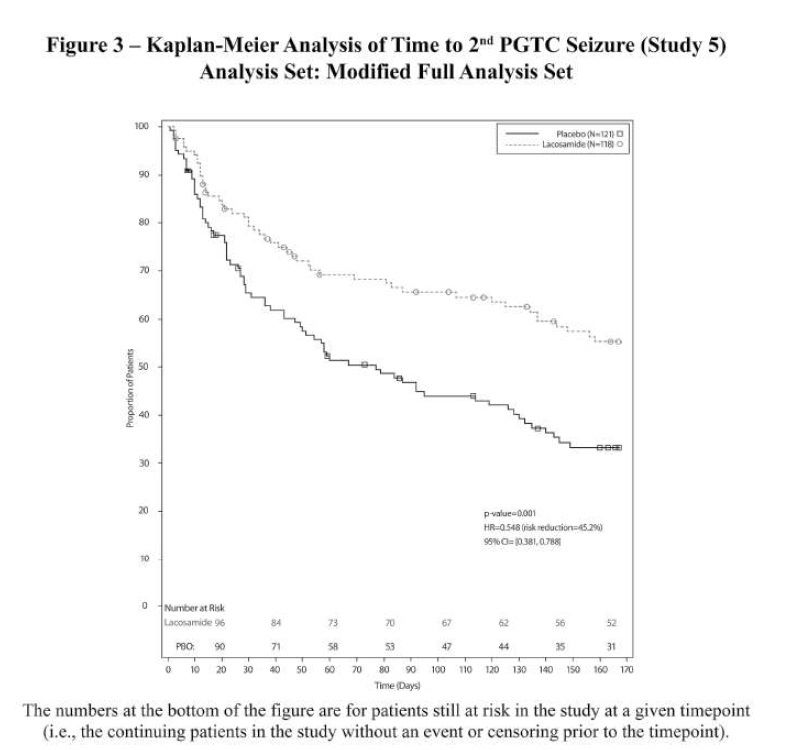 DRUG LABEL: MOTPOLY XR
NDC: 73289-0063 | Form: CAPSULE, EXTENDED RELEASE
Manufacturer: Aucta Pharmaceuticals, Inc.
Category: prescription | Type: HUMAN PRESCRIPTION DRUG LABEL
Date: 20250716
DEA Schedule: CV

ACTIVE INGREDIENTS: LACOSAMIDE 100 mg/1 1
INACTIVE INGREDIENTS: ETHYLCELLULOSE (7 MPA.S); HYPROMELLOSE 2910 (5 MPA.S); MICROCRYSTALLINE CELLULOSE; POVIDONE; TITANIUM DIOXIDE; TRIACETIN; TRIETHYL CITRATE; FERRIC OXIDE RED

HIGHLIGHTS OF PRESCRIBING INFORMATION

These highlights do not include all the information needed to use MOTPOLY XR safely and effectively. See full prescribing information for MOTPOLY XR.
MOTPOLY XR(lacosamide)™ extended-release capsules, for oral use, CV
Initial U.S. Approval: 2008

RECENT MAJOR CHANGES

Indications and Usage (1.2) 6/2024
Dosage and Administration (2.1) 6/2024

1 INDICATIONS AND USAGE

MOTPOLY XR is indicated for:

- Treatment of partial-onset seizures in adults and in pediatric patients weighing at least 50 kg (1.1)
- Adjunctive therapy in the treatment of primary generalized tonic-clonic seizures in adults and in pediatric patients weighing at least 50 kg (1.2)

2 DOSAGE AND ADMINISTRATION

- Adults (17 years and older):
  - Initial dosage for monotherapy for the treatment of partial-onset seizures is 200 mg once daily (2.1)
  - Initial dosage for adjunctive therapy for the treatment of partial-onset seizures or primary generalized tonic-clonic seizures is 100 mg once daily (2.1)
  - Maximum recommended dosage for monotherapy and adjunctive therapy is 400 mg once daily (2.1)
    - Pediatric patients weighing at least 50 kg:
      - Initial dosage for treatment of partial-onset seizures or adjunctive therapy for primary generalized tonic-clonic seizures is 100 mg once daily (2.1)
      - Increase dosage based on clinical response and tolerability, no more frequently than once per week (2.1)
      - Dose adjustment is recommended for severe renal impairment(2.1, 12.3)
      - Dose adjustment is recommended for mild or moderate hepatic impairment; use in patients with severe hepatic impairment is not recommended(2.4,12.3)
      - MOTPOLY XR capsules should be swallowed whole with liquid. Do not open, chew, or crush the capsules(2.5)

3 DOSAGE FORMS AND STRENGTHS

- 100 mg, 150 mg, 200 mg extended-release capsules (3)

4 CONTRAINDICATIONS

None (4)

5 WARNINGS AND PRECAUTIONS

- Monitor patients for suicidal behavior and ideation (5.1)
- MOTPOLY XR may cause dizziness and ataxia (5.2)
- Cardiac Rhythm and Conduction Abnormalities: Obtaining ECG before beginning and after titration to steady-state maintenance is recommended in patients with underlying proarrhythmic conditions or on concomitant medications that affect cardiac conduction; closely monitor these patients (5.3, 7.2)
- MOTPOLY XR may cause syncope (5.4)
- MOTPOLY XR should be gradually withdrawn to minimize the potential of increased seizure frequency (5.5)
- Drug Reaction with Eosinophilia and Systemic Symptoms (DRESS)/ Multi-Organ Hypersensitivity: Discontinue if no alternate etiology (5.6)

6 ADVERSE REACTIONS

- Adjunctive therapy: Most common adverse reactions in adults (≥10% and greater than placebo) are diplopia, headache, dizziness, nausea, and somnolence (6.1)
- Monotherapy: Most common adverse reactions are similar to those seen in adjunctive therapy studies (6.1)
- Pediatric patients: Adverse reactions are similar to those seen in adult patients (6.1)

To report SUSPECTED ADVERSE REACTIONS, contact Aucta Pharmaceuticals, Inc. at 1-800-655-9902 or FDA at 1-800-FDA-1088 or www.fda.gov/medwatch

8 USE IN SPECIFIC POPULATIONS

- Pregnancy: Based on animal data, may cause fetal harm (8.1)

Additional pediatric use information is approved for UCB Inc.'s Vimpat (lacosamide) tablets, oral solution, and intravenous solution. However, due to UCB Inc.'s marketing exclusivity rights, this drug product is not labeled with that pediatric information.

FULL PRESCRIBING INFORMATION

1 INDICATIONS AND USAGE

1.1 Partial-Onset Seizures

MOTPOLY XR is indicated for the treatment of partial-onset seizures in adults and in pediatric patients weighing at least 50 kg.

1.2 Primary Generalized Tonic-Clonic Seizures

MOTPOLY XR is indicated as adjunctive therapy in the treatment of primary generalized tonic-clonic seizures in adults and in pediatric patients weighing at least 50 kg.

Additional pediatric use information is approved for UCB Inc.'s Vimpat (lacosamide) tablets, oral solution, and intravenous solution. However, due to UCB Inc.'s marketing exclusivity rights, this drug product is not labeled with that pediatric information.

2 DOSAGE AND ADMINISTRATION

2.1 Dosage Information

The recommended dosage for monotherapy and adjunctive therapy for partial-onset seizures and for adjunctive therapy for primary generalized tonic-clonic seizuresin in adults and in pediatric patients weighing at least 50 kg is included in Table 1. Dosage should be increased based on clinical response and tolerability, no more frequently than once per week. Titration increments should not exceed those shown in Table 1.

Table 1: Recommended Dosages for Partial-Onset Seizures (Monotherapy or Adjunctive Therapy) and Primary Generalized Tonic-Clonic Seizures (Adjunctive Therapy) in Adults and in Pediatric Patients Weighing At Least 50 kg*
Age and Body Weight | Initial Dosage | Titration Regimen | Maintenance Dosage
Adults (17 years and older) | Monotherapy**: 200 mg once daily; Adjunctive Therapy: 100 mg once daily | Increase by 100 mg once daily every week | Monotherapy**: 300 mg to 400 mg once daily Adjunctive Therapy: 200 mg to 400 mg once daily
Pediatric patients weighing at least 50 kg | 100 mg once daily | Increase by 100 mg once daily every week | Monotherapy**: 300 mg to 400 mg once daily; Adjunctive Therapy: 200 mg to 400 mg once daily

*when not specified, the dosage is the same for monotherapy for partial-onset seizures and adjunctive therapy for partial-onset seizures or primary generalized tonic-clonic seizures .
**Monotherapy for partial-onset seizures only

In adjunctive clinical trials in adult patients with partial-onset seizures, a dosage higher than 400 mg per day was not more effective and was associated with a substantially higher rate of adverse reactions [see Adverse Reactions (6.1)and Clinical Studies (14.2)] .

Additional pediatric use information is approved for UCB Inc.'s Vimpat (lacosamide) tablets, oral solution, and intravenous solution. However, due to UCB Inc.'s marketing exclusivity rights, this drug product is not labeled with that pediatric information.

2.2 Converting From a Single Antiepileptic (AED) to MOTPOLY XR Monotherapy for the Treatment of Partial-Onset Seizures

For patients who are already on a single AED and will convert to MOTPOLY XR monotherapy, withdrawal of the concomitant AED should not occur until the therapeutic dosage of MOTPOLY XR is achieved and has been administered for at least 4 days. A gradual withdrawal of the concomitant AED over at least 6 weeks is recommended.

2.3 Dosage Information for Patients with Renal Impairment

For patients with mild to moderate renal impairment, no dosage adjustment is necessary.
For patients with severe renal impairment [creatinine clearance (CLCR) less than 30 mL/min as estimated by the Cockcroft-Gault equation for adults; CLCRless than 30 mL/min/1.73m^2as estimated by the Schwartz equation for pediatric patients] or end-stage renal disease, the maximum recommended dosage is 300 mg.
In all patients with renal impairment, dose initiation and titration should be based on clinical response and tolerability.

Hemodialysis

MOTPOLY XR is effectively removed from plasma by hemodialysis. Following a 4-hour hemodialysis treatment, dosage supplementation of up to 50% should be considered.

Concomitant Strong CYP3A4 or CYP2C9 Inhibitors

Dose reduction may be necessary in patients with renal impairment who are taking strong inhibitors of CYP3A4 and CYP2C9 [see Drug Interactions (7.1), Use in Specific Populations (8.6), and Clinical Pharmacology (12.3)] .

2.4 Dosage Information for Patients with Hepatic Impairment

For patients with mild or moderate hepatic impairment, the maximum recommended dosage is 300 mg. The dose initiation and titration should be based on clinical response and tolerability in patients with hepatic impairment. MOTPOLY XR use is not recommended in patients with severe hepatic impairment.

Concomitant Strong CYP3A4 and CYP2C9 Inhibitors

Dose reduction may be necessary in patients with hepatic impairment who are taking strong inhibitors of CYP3A4 and CYP2C9 [see Drug Interactions (7.1), Use in Specific Populations (8.7), and Clinical Pharmacology (12.3)] .

2.5 Administration Instructions for MOTPOLY XR Capsules

MOTPOLY XR may be taken with or without food.
MOTPOLY XR capsules should be swallowed whole with liquid. Do not open, chew, or crush the capsules.

2.6 Discontinuation of MOTPOLY XR

When discontinuing MOTPOLY XR, a gradual withdrawal over at least 1 week is recommended [see Warnings and Precautions (5.5)] .

3 DOSAGE FORMS AND STRENGTHS

MOTPOLY XR extended-release capsules contain white or off-white beads and are available in the following strengths:

- 100 mg: Yellow opaque cap with “A” printed in black ink and a white opaque body with “100” printed in black ink
- 150 mg: Brown opaque cap with “A” printed in black ink and a white opaque body with “150” printed in black ink
- 200 mg: Blue opaque cap with “A” printed in black ink and a white opaque body with “200” printed in black ink

4 CONTRAINDICATIONS

None .

5 WARNINGS AND PRECAUTIONS

5.1 Suicidal Behavior and Ideation

Antiepileptic drugs (AEDs), including MOTPOLY XR, increase the risk of suicidal thoughts or behavior in patients taking these drugs for any indication. Patients treated with any AED for any indication should be monitored for the emergence or worsening of depression, suicidal thoughts or behavior, and/or any unusual changes in mood or behavior.

Pooled analyses of 199 placebo-controlled clinical trials (mono- and adjunctive therapy) of 11 different AEDs showed that patients randomized to one of the AEDs had approximately twice the risk (adjusted Relative Risk 1.8, 95% CI:1.2, 2.7) of suicidal thinking or behavior compared to patients randomized to placebo. In these trials, which had a median treatment duration of 12 weeks, the estimated incidence of suicidal behavior or ideation among 27,863 AED-treated patients was 0.43%, compared to 0.24% among 16,029 placebo-treated patients, representing an increase of approximately one case of suicidal thinking or behavior for every 530 patients treated. There were four suicides in drug-treated patients in the trials and none in placebo-treated patients, but the number of events is too small to allow any conclusion about drug effect on suicide.

The increased risk of suicidal thoughts or behavior with AEDs was observed as early as one week after starting treatment with AEDs and persisted for the duration of treatment assessed. Because most trials included in the analysis did not extend beyond 24 weeks, the risk of suicidal thoughts or behavior beyond 24 weeks could not be assessed.

The risk of suicidal thoughts or behavior was generally consistent among drugs in the data analyzed. The finding of increased risk with AEDs of varying mechanisms of action and across a range of indications suggests that the risk applies to all AEDs used for any indication. The risk did not vary substantially by age (5-100 years) in the clinical trials analyzed.

Table 2 shows absolute and relative risk by indication for all evaluated AEDs.

Table 2: Risk by Indication for Antiepileptic Drugs in the Pooled Analysis
Indication | Placebo Patients with Events Per 1000 Patients | Drug Patients with Events Per 1000 Patients | Relative Risk: Incidence of Events in Drug Patients/Incidence in Placebo Patients | Risk Difference: Additional Drug Patients with Events Per 1000 Patients
Epilepsy | 1.0 | 3.4 | 3.5 | 2.4
Psychiatric | 5.7 | 8.5 | 1.5 | 2.9
Other | 1.0 | 1.8 | 1.9 | 0.9
Total | 2.4 | 4.3 | 1.8 | 1.9

The relative risk for suicidal thoughts or behavior was higher in clinical trials for epilepsy than in clinical trials for psychiatric or other conditions, but the absolute risk differences were similar.

Anyone considering prescribing MOTPOLY XR or any other AED must balance this risk with the risk of untreated illness. Epilepsy and many other illnesses for which antiepileptics are prescribed are themselves associated with morbidity and mortality and an increased risk of suicidal thoughts and behavior. Should suicidal thoughts and behavior emerge during treatment, the prescriber needs to consider whether the emergence of these symptoms in any given patient may be related to the illness being treated.

5.2 Dizziness and Ataxia

MOTPOLY XR may cause dizziness and ataxia in adult and pediatric patients. In adult patients with partial-onset seizures taking 1 to 3 concomitant AEDs, dizziness was experienced by 25% of patients randomized to the recommended doses (200 to 400 mg/day) of lacosamide (compared with 8% of placebo patients) and was the adverse reaction most frequently leading to discontinuation (3%). Ataxia was experienced by 6% of patients randomized to the recommended doses (200 to 400 mg/day) of lacosamide (compared to 2% of placebo patients). The onset of dizziness and ataxia was most commonly observed during titration. There was a substantial increase in these adverse events at doses higher than 400 mg/day [ see Adverse Reactions (6.1)] .

5.3 Cardiac Rhythm and Conduction Abnormalities

PR Interval Prolongation, Atrioventricular Block, and Ventricular Tachyarrhythmia

Dose-dependent prolongations in PR interval have been observed in clinical studies of lacosamide, the active moiety in MOTPOLY XR, in adult patients and in healthy volunteers [ see Clinical Pharmacology (12.2)] . In adjunctive clinical trials in adult patients with partial-onset seizures, asymptomatic first-degree atrioventricular (AV) block was observed as an adverse reaction in 0.4% (4/944) of patients randomized to receive lacosamide and 0% (0/364) of patients randomized to receive placebo. One case of profound bradycardia was observed in a patient during a 15-minute infusion of 150 mg lacosamide. When MOTPOLY XR is given with other drugs that prolong the PR interval, further PR prolongation is possible.

In the postmarketing setting, there have been reports of cardiac arrhythmias in patients treated with lacosamide, including bradycardia, AV block, and ventricular tachyarrhythmia, which have rarely resulted in asystole, cardiac arrest, and death. Most, although not all, cases have occurred in patients with underlying proarrhythmic conditions, or in those taking concomitant medications that affect cardiac conduction or prolong the PR interval. These events have occurred with both oral and intravenous routes of administration and at prescribed doses as well as in the setting of overdose [ see Overdosage (10)] .

MOTPOLY XR should be used with caution in patients with underlying proarrhythmic conditions such as known cardiac conduction problems (e.g., marked first-degree AV block, second-degree or higher AV block and sick sinus syndrome without pacemaker), severe cardiac disease (e.g., myocardial ischemia or heart failure, or structural heart disease), and cardiac sodium channelopathies (e.g., Brugada Syndrome). MOTPOLY XR should also be used with caution in patients on concomitant medications that affect cardiac conduction, including sodium channel blockers, beta-blockers, calcium channel blockers, potassium channel blockers, and medications that prolong the PR interval [s ee Drug Interactions (7.2)] . In such patients, obtaining an ECG before beginning MOTPOLY XR, and after MOTPOLY XR is titrated to steady-state maintenance dose, is recommended.

Atrial Fibrillation and Atrial Flutter

In the short-term investigational trials of lacosamide in adult patients with partial-onset seizures there were no cases of atrial fibrillation or flutter. Both atrial fibrillation and atrial flutter have been reported in open label partial-onset seizure trials and in postmarketing experience. In adult patients with diabetic neuropathy, for which lacosamide is not indicated, 0.5% of patients treated with lacosamide experienced an adverse reaction of atrial fibrillation or atrial flutter, compared to 0% of placebo-treated patients. MOTPOLY XR administration may predispose to atrial arrhythmias (atrial fibrillation or flutter), especially in patients with diabetic neuropathy and/or cardiovascular disease.

5.4 Syncope

In the short-term controlled trials of lacosamide in adult patients with partial-onset seizures with no significant system illnesses, there was no increase in syncope compared to placebo. In the short-term controlled trials in adult patients with diabetic neuropathy, for which lacosamide is not indicated, 1.2% of patients who were treated with lacosamide reported an adverse reaction of syncope or loss of consciousness, compared with 0% of placebo-treated patients with diabetic neuropathy. Most of the cases of syncope were observed in patients receiving doses above 400 mg/day. The cause of syncope was not determined in most cases. However, several were associated with either changes in orthostatic blood pressure, atrial flutter/fibrillation (and associated tachycardia), or bradycardia. Cases of syncope have also been observed in open-label clinical partial-onset seizure studies in adult and pediatric patients. These cases were associated with a history of risk factors for cardiac disease and the use of drugs that slow AV conduction.

5.5 Withdrawal of Antiepileptic Drugs (AEDs)

As with all AEDs, MOTPOLY XR should be withdrawn gradually (over a minimum of 1 week) to minimize the potential of increased seizure frequency in patients with seizure disorders.

5.6 Drug Reaction with Eosinophilia and Systemic Symptoms (DRESS)/Multi-Organ Hypersensitivity

Drug Reaction with Eosinophilia and Systemic Symptoms (DRESS), also known as multi-organ hypersensitivity, has been reported in patients taking antiepileptic drugs, including including lacosamide, the active moiety in MOTPOLY XR. Some of these events have been fatal or life-threatening. DRESS typically, although not exclusively, presents with fever, rash, lymphadenopathy and/or facial swelling, in association with other organ system involvement, such as hepatitis, nephritis, hematologic abnormalities, myocarditis, or myositis, sometimes resembling an acute viral infection. Eosinophilia is often present. This disorder is variable in its expression, and other organ systems not noted here may be involved. It is important to note that early manifestations of hypersensitivity (e.g., fever, lymphadenopathy) may be present even though rash is not evident. If such signs or symptoms are present, the patient should be evaluated immediately. MOTPOLY XR should be discontinued if an alternative etiology for the signs or symptoms cannot be established.

6 ADVERSE REACTIONS

The following serious adverse reactions are described below and elsewhere in the labeling:

- Suicidal Behavior and Ideation [ see Warnings and Precautions (5.1)]
- Dizziness and Ataxia [ see Warnings and Precautions (5.2)]
- Cardiac Rhythm and Conduction Abnormalities [ see Warnings and Precautions (5.3)]
- Syncope [ see Warnings and Precautions (5.4)]
- Drug Reaction with Eosinophilia and Systemic Symptoms (DRESS)/Multiorgan Hypersensitivity Reactions [ see Warnings and Precautions (5.6)]

6.1 Clinical Trials Experience

Because clinical trials are conducted under widely varying conditions, adverse reaction rates observed in the clinical trials of a drug cannot be directly compared to rates in the clinical trials of another drug and may not reflect the rates observed in practice.

The studies described below were conducted with immediate-release lacosamide tablets; adverse reactions with MOTPOLY XR are expected to be similar to adverse reactions with immediate-release lacosamide.

Lacosamide in Adults

In the premarketing development of adjunctive therapy for partial-onset seizures, 1327 adult patients received lacosamide in controlled and uncontrolled trials, of whom 1000 were treated for longer than 6 months, and 852 for longer than 12 months. The monotherapy development program for partial-onset seizures included 425 adult patients, 310 of whom were treated for longer than 6 months, and 254 for longer than 12 months.

Partial-Onset Seizures

Monotherapy Historical-Control Trial (Study 1)

In the monotherapy trial for partial-onset seizures, 16% of patients randomized to receive lacosamide at the recommended doses of 300 and 400 mg/day discontinued from the trial as a result of an adverse reaction. The adverse reaction most commonly (≥1% on lacosamide) leading to discontinuation was dizziness.

Adverse reactions that occurred in this study were generally similar to those that occurred in adjunctive placebo-controlled studies. One adverse reaction, insomnia, occurred at a rate of ≥2% and was not reported at a similar rate in previous studies. This adverse reaction has also been observed in postmarketing experience [ see Adverse Reactions (6.2)] . Because this study did not include a placebo control group, causality could not be established.

Dizziness, headache, nausea, somnolence, and fatigue all occurred at lower incidences during the AED Withdrawal Phase and Monotherapy Phase, compared with the Titration Phase [ see Clinical Studies (14.1)] .

Adjunctive Therapy Controlled Trials (Studies 2, 3, and 4)

In adjunctive therapy controlled clinical trials for partial-onset seizures, the rate of discontinuation as a result of an adverse reaction was 8% and 17% in patients randomized to receive lacosamide at the recommended doses of 200 and 400 mg/day, respectively, 29% at 600 mg/day (1.5 times greater than the maximum recommended dose), and 5% in patients randomized to receive placebo. The adverse reactions most commonly (>1% on lacosamide and greater than placebo) leading to discontinuation were dizziness, ataxia, vomiting, diplopia, nausea, vertigo, and blurred vision.

Table 3 gives the incidence of adverse reactions that occurred in ≥2% of adult patients with partial-onset seizures in the lacosamide total group and for which the incidence was greater than placebo.

Table 3: Adverse Reactions Incidence in Adjunctive Therapy Pooled, Placebo-Controlled Trials in Adult Patients with Partial-Onset Seizures (Studies 2, 3, and 4)
Adverse Reaction | Placebo N=364 % | Lacosamide 200 mg/day N=270 % | Lacosamide 400 mg/day N=471 % | Lacosamide 600 mg/day [600 mg dose is 1.5 times greater than the maximum recommended dose.] N=203 % | Lacosamide Total N=944 %
Ear and labyrinth disorder
Vertigo | 1 | 5 | 3 | 4 | 4
Eye disorders
Diplopia | 2 | 6 | 10 | 16 | 11
Blurred Vision | 3 | 2 | 9 | 16 | 8
Gastrointestinal disorders
Nausea | 4 | 7 | 11 | 17 | 11
Vomiting | 3 | 6 | 9 | 16 | 9
Diarrhea | 3 | 3 | 5 | 4 | 4
General disorders and administration site conditions
Fatigue | 6 | 7 | 7 | 15 | 9
Gait disturbance | <1 | <1 | 2 | 4 | 2
Asthenia | 1 | 2 | 2 | 4 | 2
Injury, poisoning and procedural complications
Contusion | 3 | 3 | 4 | 2 | 3
Skin laceration | 2 | 2 | 3 | 3 | 3
Nervous system disorders
Dizziness | 8 | 16 | 30 | 53 | 31
Headache | 9 | 11 | 14 | 12 | 13
Ataxia | 2 | 4 | 7 | 15 | 8
Somnolence | 5 | 5 | 8 | 8 | 7
Tremor | 4 | 4 | 6 | 12 | 7
Nystagmus | 4 | 2 | 5 | 10 | 5
Balance disorder | 0 | 1 | 5 | 6 | 4
Memory impairment | 2 | 1 | 2 | 6 | 2
Psychiatric disorders
Depression | 1 | 2 | 2 | 2 | 2
Skin and subcutaneous disorders
Pruritus | 1 | 3 | 2 | 3 | 2

The overall adverse reaction rate was similar in male and female patients. Although there were few non-Caucasian patients, no differences in the incidences of adverse reactions compared to Caucasian patients were observed.

Lacosamide in Pediatric Patients
Safety of lacosamide was evaluated in clinical studies of pediatric patients for the treatment of partial-onset seizures. Across studies in pediatric patients with partial-onset seizures, 328 patients received lacosamide, of whom 148 received lacosamide for at least 1 year. Adverse reactions reported in clinical studies of pediatric patients were similar to those seen in adult patients.

Primary Generalized Tonic-Clonic Seizures in Patients Adjunctive Therapy Trial (Study 5)

In the adjunctive therapy placebo-controlled trial for primary generalized tonic-clonic seizures, adverse reactions that occurred in the study were generally similar to those that occurred in partial-onset seizure placebo-controlled studies. The most common adverse reactions (≥ 10% on lacosamide) reported in patients treated with lacosamide were dizziness (23%), somnolence (17%), headache (14%), and nausea (10%), compared to 7%, 14%, 10%, and 6%, respectively, of patients who received placebo. Additionally, an adverse reaction not previously reported of myoclonic epilepsy was reported in 3% of patients treated with lacosamide compared to 1% of patients who received placebo. It is also noted that 2 patients receiving lacosamide had acute worsening of seizures shortly after drug initiation, including one episode of status epilepticus, compared to no patients receiving placebo.

Laboratory Abnormalities

Abnormalities in liver function tests have occurred in controlled trials with lacosamide in adult patients with partial-onset seizures who were taking 1 to 3 concomitant anti-epileptic drugs. Elevations of ALT to ≥3x ULN occurred in 0.7% (7/935) of lacosamide patients and 0% (0/356) of placebo patients. One case of hepatitis with transaminases >20x ULN occurred in one healthy subject 10 days after lacosamide treatment completion, along with nephritis (proteinuria and urine casts). Serologic studies were negative for viral hepatitis. Transaminases returned to normal within one month without specific treatment. At the time of this event, bilirubin was normal. The hepatitis/nephritis was interpreted as a delayed hypersensitivity reaction to lacosamide.

Other Adverse Reactions

The following is a list of adverse reactions reported by patients treated with lacosamide in all clinical trials in adult patients, including controlled trials and long-term open-label extension trials. Adverse reactions addressed in other tables or sections are not listed here.

Blood and lymphatic system disorders: neutropenia, anemia

Cardiac disorders: palpitations

Ear and labyrinth disorders: tinnitus

Gastrointestinal disorders: constipation, dyspepsia, dry mouth, oral hypoaesthesia

General disorders and administration site conditions: irritability, pyrexia, feeling drunk

Injury, poisoning, and procedural complications: fall

Musculoskeletal and connective tissue disorders: muscle spasms

Nervous system disorders: paresthesia, cognitive disorder, hypoaesthesia, dysarthria, disturbance in attention, cerebellar syndrome

Psychiatric disorders: confusional state, mood altered, depressed mood

6.2 Postmarketing Experience

The following adverse reactions have been identified during post-approval use of lacosamide. Because these reactions are reported voluntarily from a population of uncertain size, it is not always possible to reliably estimate their frequency or establish a causal relationship to drug exposure.

Blood and lymphatic system disorders: Agranulocytosis
Psychiatric disorders: Aggression, agitation, hallucination, insomnia, psychotic disorder
Skin and subcutaneous tissue disorders: Angioedema, rash, urticaria, Stevens-Johnson syndrome, toxic epidermal necrolysis
Neurologic disorders: Dyskinesia, new or worsening seizures

7 DRUG INTERACTIONS

7.1 Strong CYP3A4 or CYP2C9 Inhibitors

Patients with renal or hepatic impairment who are taking strong inhibitors of CYP3A4 and CYP2C9 may have a significant increase in exposure to MOTPOLY XR. Dose reduction may be necessary in these patients.

7.2 Concomitant Medications that Affect Cardiac Conduction

MOTPOLY XR should be used with caution in patients on concomitant medications that affect cardiac conduction (sodium channel blockers, beta-blockers, calcium channel blockers, potassium channel blockers) including those that prolong PR interval (including sodium channel blocking AEDs), because of a risk of AV block, bradycardia, or ventricular tachyarrhythmia. In such patients, obtaining an ECG before beginning MOTPOLY XR, and after MOTPOLY XR is titrated to steady-state, is recommended.

7.3 CNS Depressants

Concomitant administration of lacosamide and alcohol or other CNS depressant drugs has not been evaluated in clinical studies. Because of the potential of MOTPOLY XR to cause CNS depression, as well as other cognitive and/or neuropsychiatric adverse reactions, MOTPOLY XR should be used with extreme caution if used in combination with alcohol and other CNS depressants.

8 USE IN SPECIFIC POPULATIONS

8.1 Pregnancy

Pregnancy Exposure Registry

There is a pregnancy exposure registry that monitors pregnancy outcomes in women exposed to antiepileptic drugs (AEDs), such as lacosamide, during pregnancy. Encourage women who are taking MOTPOLY XR during pregnancy to enroll in the North American Antiepileptic Drug (NAAED) pregnancy registry by calling 1-888-233-2334 or visiting http://www.aedpregnancyregistry.org/.

Risk Summary

Available data from the North American Antiepileptic Drug (NAAED) pregnancy registry, a prospective cohort study, case reports, and a case series with lacosamide use in pregnant women are insufficient to identify a drug associated risk of major birth defects, miscarriage or other adverse maternal or fetal outcomes. There are no adequate data on the developmental risks associated with the use of MOTPOLY XR in pregnant women. Lacosamide produced developmental toxicity (increased embryofetal and perinatal mortality, growth deficit) in rats following administration during pregnancy. Developmental neurotoxicity was observed in rats following administration during a period of postnatal development corresponding to the third trimester of human pregnancy. These effects were observed at doses associated with clinically relevant plasma exposures (see Data).

The background risk of major birth defects and miscarriage for the indicated population is unknown. All pregnancies have a background risk of birth defect, loss, or other adverse outcomes. In the U.S. general population the estimated background risk of major birth defects and miscarriage in clinically recognized pregnancies is 2-4% and 15-20%, respectively.

Data

Animal Data

Oral administration of lacosamide to pregnant rats (20, 75, or 200 mg/kg/day) and rabbits (6.25, 12.5, or 25 mg/kg/day) during the period of organogenesis did not produce any effects on the incidences of fetal structural abnormalities. However, the maximum doses evaluated were limited by maternal toxicity in both species and embryofetal death in rats. These doses were associated with maternal plasma lacosamide exposures (AUC) approximately 2 and 1 times (rat and rabbit, respectively) that in humans at the maximum recommended human dose (MRHD) of 400 mg/day.

In two studies in which lacosamide (25, 70, or 200 mg/kg/day and 50, 100, or 200 mg/kg/day) was orally administered to rats throughout pregnancy and lactation, increased perinatal mortality and decreased body weights in the offspring were observed at the highest dose tested. The no-effect dose for pre- and postnatal developmental toxicity in rats (70 mg/kg/day) was associated with a maternal plasma lacosamide AUC similar to that in humans at the MRHD.

Oral administration of lacosamide (30, 90, or 180 mg/kg/day) to rats during the neonatal and juvenile periods of development resulted in decreased brain weights and long-term neurobehavioral changes (altered open field performance, deficits in learning and memory). The early postnatal period in rats is generally thought to correspond to late pregnancy in humans in terms of brain development. The no-effect dose for developmental neurotoxicity in rats was associated with a plasma lacosamide AUC less than that in humans at the MRHD.

In Vitro Data

Lacosamide has been shown in vitroto interfere with the activity of collapsin response mediator protein-2 (CRMP-2), a protein involved in neuronal differentiation and control of axonal outgrowth. Potential adverse effects on CNS development related to this activity cannot be ruled out.

8.2 Lactation

Risk Summary

Data from published literature indicate that lacosamide is present in human milk. There are reports of increased sleepiness in breastfed infants exposed to lacosamide (see Clinical Considerations). There is no information on the effects of lacosamide on milk production.

The developmental and health benefits of breastfeeding should be considered along with the mother’s clinical need for MOTPOLY XR and any potential adverse effects on the breastfed infant from MOTPOLY XR or from the underlying maternal condition.

Clinical Considerations
Monitor infants exposed to lacosamide through breastmilk for excess sedation.

8.4 Pediatric Use

Partial-Onset Seizures

The safety and effectiveness of MOTPOLY XR for the treatment of partial-onset seizures have been established in pediatric patients weighing at least 50 kg. Use of MOTPOLY XR in this pediatric group is supported by evidence from adequate and well-controlled studies of lacosamide in adults with partial-onset seizures, pharmacokinetic data from adult and pediatric patients, and safety data in 328 pediatric patients [ see Adverse Reactions (6.1) and Clinical Pharmacology (12.3)and Clinical Studies (14.1, 14.2) ].

Safety and effectiveness of MOTPOLY XR in pediatric patients weighing less than 50 kg have not been established.

Primary Generalized Tonic-Clonic Seizures
Safety and effectiveness of MOTPOLY XR as adjunctive therapy in the treatment of primary generalized tonic-clonic seizures in pediatric patients with idiopathic generalized epilepsy weighing at least 50 kg was established in a 24-week double-blind, randomized, placebo-controlled, parallel-group, multi-center study (Study 5), which included pediatric patients [see Adverse Reactions (6.1), Clinical Pharmacology (12.3) and Clinical Studies (14.1, 14.3)].

Safety and effectiveness in pediatric patients weighing less than 50 kg have not been established.

Additional pediatric use information is approved for UCB Inc.'s Vimpat (lacosamide) tablets, oral solution, and intravenous solution. However, due to UCB Inc.'s marketing exclusivity rights, this drug product is not labeled with that pediatric information.

Animal Data
Lacosamide has been shown in vitro to interfere with the activity of collapsin response mediator protein-2 (CRMP-2), a protein involved in neuronal differentiation and control of axonal outgrowth. Potential related adverse effects on CNS development cannot be ruled out. Administration of lacosamide to rats during the neonatal and juvenile periods of postnatal development (approximately equivalent to neonatal through adolescent development in humans) resulted in decreased brain weights and long-term neurobehavioral changes (altered open field performance, deficits in learning and memory). The no-effect dose for developmental neurotoxicity in rats was associated with a plasma lacosamide exposure (AUC) less than that in humans at the maximum recommended human dose of 400 mg/day.

8.5 Geriatric Use

There were insufficient numbers of elderly patients enrolled in partial-onset seizure trials (n=18) to adequately determine whether they respond differently from younger patients.

No MOTPOLY XR dose adjustment based on age is necessary. In elderly patients, dose titration should be performed with caution, usually starting at the lower end of the dosing range, reflecting the greater frequency of decreased hepatic function, decreased renal function, increased cardiac conduction abnormalities, and polypharmacy [see Dosage and Administration (2.1, 2.3, 2.4) and Clinical Pharmacology (12.3)] .

8.6 Renal Impairment

No dose adjustment is necessary in patients with mild to moderate renal impairment (CLCR≥30 mL/min). In patients with severe renal impairment [creatinine clearance (CLCR) less than 30 mL/min as estimated by the Cockcroft-Gault equation for adults; CLCR less than 30 mL/min/1.73m^2as estimated by the Schwartz equation for pediatric patients ] and in those with end-stage renal disease, the maximum recommended dosage is 300 mg once daily [see Dosage and Administration (2.3)and Clinical Pharmacology (12.3)] .

In all patients with renal impairment, dose initiation and titration should be based on clinical response and tolerability.

MOTPOLY XR is effectively removed from plasma by hemodialysis. Dosage supplementation of up to 50% following hemodialysis should be considered.

8.7 Hepatic Impairment

For adult and pediatric patients with mild to moderate hepatic impairment, the maximum recommended dosage is 300 mg once daily. Patients with mild to moderate hepatic impairment should be observed closely for adverse reactions, and dose initiation and titration should be based on clinical response and tolerability [see Dosage and Administration (2.4), Clinical Pharmacology (12.3)] .

The pharmacokinetics of lacosamide has not been evaluated in severe hepatic impairment. MOTPOLY XR use is not recommended in patients with severe hepatic impairment.

9 DRUG ABUSE AND DEPENDENCE

9.1 Controlled Substance

MOTPOLY XR contains lacosamide, a Schedule V controlled substance.

9.2 Abuse

Abuse is the intentional, non-therapeutic use of a drug, even once, for its desirable psychological or physiological effects. In a human abuse potential study, single doses of 200 mg and 800 mg lacosamide (equal to and 2 times the recommended maintenance dosage, respectively) produced euphoria-type subjective responses that differentiated statistically from placebo; at 800 mg, these euphoria-type responses were statistically indistinguishable from those produced by alprazolam, a Schedule IV drug. The duration of the euphoria-type responses following lacosamide was less than that following alprazolam. A high rate of euphoria was also reported as an adverse event in the human abuse potential study following single doses of 800 mg lacosamide (15% [5/34]) compared to placebo (0%) and in two pharmacokinetic studies following single and multiple doses of 300-800 mg lacosamide (ranging from 6% [2/33] to 25% [3/12]) compared to placebo (0%). However, the rate of euphoria reported as an adverse event in the lacosamide development program at therapeutic doses was less than 1%.

9.3 Dependence

Physical dependence is a state that develops as a result of physiological adaptation in response to repeated drug use, manifested by withdrawal signs and symptoms after abrupt discontinuation or a significant dose reduction of a drug. Abrupt termination of lacosamide in clinical trials with diabetic neuropathic pain patients produced no signs or symptoms that are associated with a withdrawal syndrome indicative of physical dependence. However, psychological dependence cannot be excluded due to the ability of lacosamide to produce euphoria-type adverse events in humans.

10 OVERDOSAGE

Events reported after an intake of more than 800 mg (twice the maximum recommended daily dosage) of lacosamide include dizziness, nausea, and seizures (generalized tonic-clonic seizures, status epilepticus). Cardiac conduction disorders, confusion, decreased level of consciousness, cardiogenic shock, cardiac arrest, and coma have also been observed. Fatalities have occurred following lacosamide overdoses of several grams.

There is no specific antidote for overdose with lacosamide. Standard decontamination procedures should be followed. General supportive care of the patient is indicated including monitoring of vital signs and observation of the clinical status of patient. A Certified Poison Control Center should be contacted for up to date information on the management of overdose with lacosamide.

Standard hemodialysis procedures result in significant clearance of lacosamide (reduction of systemic exposure by 50% in 4 hours). Hemodialysis may be indicated based on the patient's clinical state or in patients with significant renal impairment.

11 DESCRIPTION

The chemical name of lacosamide, the single (R)-enantiomer, is (R)-2-acetamido-N-benzyl-3-methoxypropionamide (IUPAC). Lacosamide is a functionalized amino acid. Its molecular formula is C13H18N2O3and its molecular weight is 250.30. The chemical structure is:

Lacosamide is a white to light yellow powder. It is sparingly soluble in water and slightly soluble in acetonitrile and ethanol.

MOTPOLY XR extended-release capsules for oral administration contain lacosamide and the following inactive ingredients: ethylcellulose, hypromellose, microcrystalline cellulose, povidone, titanium dioxide, triacetin, triethyl citrate and dye pigments as specified below:

The capsule shells contain the following coloring agents:
100 mg capsules: red iron oxide
150 mg capsules: red iron oxide, yellow iron oxide
200 mg capsules: black iron oxide, FD&C Blue #1, red iron oxide

12 CLINICAL PHARMACOLOGY

12.1 Mechanism of Action

The precise mechanism by which MOTPOLY XR exerts its antiepileptic effects in humans remains to be fully elucidated. In vitro electrophysiological studies have shown that lacosamide selectively enhances slow inactivation of voltage-gated sodium channels, resulting in stabilization of hyperexcitable neuronal membranes and inhibition of repetitive neuronal firing.

12.2 Pharmacodynamics

A pharmacokinetic-pharmacodynamic (efficacy) analysis was performed based on the pooled data from the 3 efficacy trials for partial-onset seizures. Lacosamide exposure is correlated with the reduction in seizure frequency. However, doses above 400 mg/day do not appear to confer additional benefit in group analyses.

Cardiac Electrophysiology

Electrocardiographic effects of lacosamide were determined in a double-blind, randomized clinical pharmacology trial of 247 healthy subjects. Chronic oral doses of 400 and 800 mg/day(equal to and two times the maximum recommended dose, respectively) were compared with placebo and a positive control (400 mg moxifloxacin). Lacosamide did not prolong QTc interval and did not have a dose-related or clinically important effect on QRS duration. Lacosamide produced a small, dose-related increase in mean PR interval. At steady-state, the time of the maximum observed mean PR interval corresponded with tmax. The placebo-subtracted maximum increase in PR interval (at tmax) was 7.3 ms for the 400 mg/day group and 11.9 ms for the 800 mg/day group. For patients who participated in the controlled trials, the placebo-subtracted mean maximum increase in PR interval for a 400 mg/day lacosamide dose was 3.1 ms in patients with partial-onset seizures and 9.4 ms for patients with diabetic neuropathy.

12.3 Pharmacokinetics

Absorption
Pharmacokinetic information for MOTPOLY XR following oral administration was obtained from studies conducted in healthy adult subjects.

Lacosamide is completely absorbed after oral administration with negligible first-pass effect with a high absolute bioavailability of approximately 100%. In a multiple-dose pharmacokinetic study in healthy adult subjects, at steady-state, the peak plasma lacosamide concentrations (Tmax) after oral administration of MOTPOLY XR was reached in 7 hours. Steady state plasma concentrations are achieved after 4 days of once daily repeated administration. Pharmacokinetics of lacosamide are dose proportional (100-800 mg).

Effect of Food

Compared to the fasted state, high-fat meal has no effect on the Cmax, Tmaxand AUC of MOTPOLY XR. [see Dosage and Administration (2.5)].

Distribution
The volume of distribution is approximately 0.67 L/kg, which is close to the volume of total body water. Lacosamide is less than 15% bound to plasma proteins.

Metabolism and Elimination

Lacosamide is primarily eliminated from the systemic circulation by renal excretion and biotransformation.

After oral and intravenous administration of 100 mg [14C]-lacosamide approximately 95% of radioactivity administered was recovered in the urine and less than 0.5% in the feces. The major compounds excreted were unchanged lacosamide (approximately 40% of the dose), its O-desmethyl metabolite (approximately 30%), and a structurally unknown polar fraction (~20%). The plasma exposure of the major human metabolite, O-desmethyl-lacosamide, is approximately 10% of that of lacosamide. This metabolite has no known pharmacological activity.

The CYP isoforms mainly responsible for the formation of the major metabolite (O-desmethyl) are CYP3A4, CYP2C9, and CYP2C19. The elimination half-life of the unchanged drug is approximately 13 hours and is not altered by different doses, multiple dosing or intravenous administration.

There is no enantiomeric interconversion of lacosamide.

Specific Populations

Renal Impairment

Lacosamide and its major metabolite are eliminated from the systemic circulation primarily by renal excretion.

The AUC of lacosamide was increased approximately 25% in mildly (CLCR50-80 mL/min) and moderately (CLCR30-50 mL/min) and 60% in severely (CLCR≤30 mL/min) renally impaired patients compared to subjects with normal renal function (CLCR>80 mL/min), whereas Cmaxwas unaffected. Lacosamide is effectively removed from plasma by hemodialysis. Following a 4-hour hemodialysis treatment, AUC of lacosamide is reduced by approximately 50% [see Dosage and Administration (2.3)] .

Hepatic Impairment

Lacosamide undergoes metabolism. Subjects with moderate hepatic impairment (Child-Pugh B) showed higher plasma concentrations of lacosamide (approximately 50-60% higher AUC compared to healthy subjects). The pharmacokinetics of lacosamide have not been evaluated in severe hepatic impairment [see Dosage and Administration (2.4)] .

Pediatric Patients

The pediatric pharmacokinetic profile of lacosamide was determined in a population pharmacokinetic analysis using sparse plasma concentration data obtained in two open-label studies in 79 pediatric patients with partial-onset seizures that included patients weighing at least 50 kg. The recommended dosing regimen of MOTPOLY XR in pediatric patients weighing at least 50 kg is necessary to achieve lacosamide exposures
similar to those observed in adults treated at effective doses of lacosamide [ see Dosage and Administration (2.1)].

The pharmacokinetics of lacosamide in pediatric patients are similar when used as monotherapy or as adjunctive therapy for the treatment of partial-onset seizures and as adjunctive therapy for the treatment of primary generalized tonic-clonic seizures.

Geriatric Patients

In the elderly (>65 years), dose and body-weight normalized AUC and Cmaxis about 20% increased compared to young subjects (18-64 years). This may be related to body weight and decreased renal function in elderly subjects.

Gender

Lacosamide clinical trials indicate that gender does not have a clinically relevant influence on the pharmacokinetics of lacosamide.

Race

There are no clinically relevant differences in the pharmacokinetics of lacosamide between Asian, Black, and Caucasian subjects.

CYP2C19 Polymorphism

There are no clinically relevant differences in the pharmacokinetics of lacosamide between CYP2C19 poor metabolizers and extensive metabolizers [ see Pharmacogenomics (12.5) ].

Drug Interactions

In Vitro Assessment of Drug Interactions

In vitrometabolism studies indicate that lacosamide does not induce the enzyme activity of drug metabolizing cytochrome P450 isoforms CYP1A2, 2B6, 2C9, 2C19 and 3A4. Lacosamide did not inhibit CYP 1A1, 1A2, 2A6, 2B6, 2C8, 2C9, 2D6, 2E1, 3A4/5 at plasma concentrations observed in clinical studies.

In vitrodata suggest that lacosamide has the potential to inhibit CYP2C19 at therapeutic concentrations. However, an in vivostudy with omeprazole did not show an inhibitory effect on omeprazole pharmacokinetics.

Lacosamide was not a substrate or inhibitor for P-glycoprotein.

Lacosamide is a substrate of CYP3A4, CYP2C9, and CYP2C19. Patients with renal or hepatic impairment who are taking strong inhibitors of CYP3A4 and CYP2C9 may have increased exposure to lacosamide.

Since <15% of lacosamide is bound to plasma proteins, a clinically relevant interaction with other drugs through competition for protein binding sites is unlikely.

In Vivo Assessment of Drug Interactions

- Drug interaction studies with AEDs
  - Effect of Lacosamide on concomitant AEDs
    Lacosamide 400 mg/day had no influence on the pharmacokinetics of 600 mg/day valproic acid and 400 mg/day carbamazepine in healthy subjects.
    The placebo-controlled clinical studies in patients with partial-onset seizures showed that steady-state plasma concentrations of levetiracetam, carbamazepine, carbamazepine epoxide, lamotrigine, topiramate, oxcarbazepine monohydroxy derivative (MHD), phenytoin, valproic acid, phenobarbital, gabapentin, clonazepam, and zonisamide were not affected by concomitant intake of lacosamideat any dose.
  - Effect of concomitant AEDs on Lacosamide
    Drug-drug interaction studies in healthy subjects showed that 600 mg/day valproic acid had no influence on the pharmacokinetics of 400 mg/daylacosamide. Likewise, 400 mg/day carbamazepine had no influence on the pharmacokinetics of lacosamidein a healthy subject study. Population pharmacokinetics results in patients with partial-onset seizures showed small reductions (15% to 20% lower) in lacosamide plasma concentrations when lacosamide was coadministered with carbamazepine, phenobarbital or phenytoin.
- Drug-drug interaction studies with other drugs
  - Digoxin
    There was no effect of lacosamide (400 mg/day) on the pharmacokinetics of digoxin (0.5 mg once daily) in a study in healthy subjects.
  - Metformin
    There were no clinically relevant changes in metformin levels following coadministration of lacosamide (400 mg/day).
    Metformin (500 mg three times a day) had no effect on the pharmacokinetics of lacosamide (400 mg/day).
  - Omeprazole
    Omeprazole is a CYP2C19 substrate and inhibitor.
    There was no effect of lacosamide (600 mg/day) on the pharmacokinetics of omeprazole (40 mg single dose) in healthy subjects. The data indicated that lacosamide had little in vivoinhibitory or inducing effect on CYP2C19.
    Omeprazole at a dose of 40 mg once daily had no effect on the pharmacokinetics of lacosamide (300 mg single dose). However, plasma levels of the O-desmethyl metabolite were reduced about 60% in the presence of omeprazole.
  - Midazolam
    Midazolam is a 3A4 substrate.
    There was no effect of lacosamide (200 mg single dose or repeat doses of 400 mg/day given as 200 mg BID) on the pharmacokinetics of midazolam (single dose, 7.5 mg), indicating no inhibitory or inducing effects on CYP3A4.
  - Oral Contraceptives
    There was no influence of lacosamide(400 mg/day) on the pharmacodynamics and pharmacokinetics of an oral contraceptive containing 0.03 mg ethinylestradiol and 0.15 mg levonorgestrel in healthy subjects, except that a 20% increase in ethinylestradiol Cmaxwas observed.
  - Warfarin
    Co-administration of lacosamide (400 mg/day) with warfarin (25 mg single dose) did not result in a clinically relevant change in the pharmacokinetic and pharmacodynamic effects of warfarin in a study in healthy male subjects.

12.5 Pharmacogenomics

Results from a trial in poor metabolizers (PM) (N=4) and extensive metabolizers (EM) (N=8) of cytochrome P450 (CYP) 2C19 showed that lacosamide plasma concentrations were similar in PMs and EMs, but plasma concentrations and the amount excreted into urine of the O-desmethyl metabolite were about 70% reduced in PMs compared to EMs. This difference is not clinically significant [ see Clinical Pharmacology (12.3)] .

13 NONCLINICAL TOXICOLOGY

13.1 Carcinogenesis, Mutagenesis, Impairment of Fertility

Carcinogenesis

There was no evidence of drug related carcinogenicity in mice or rats. Mice and rats received lacosamide once daily by oral administration for 104 weeks at doses producing plasma exposures (AUC) up to approximately 1 and 3 times, respectively, the plasma AUC in humans at the maximum recommended human dose (MRHD) of 400 mg/day.

Mutagenesis

Lacosamide was negative in an in vitroAmes test and an in vivomouse micronucleus assay. Lacosamide induced a positive response in the in vitromouse lymphoma assay.

Fertility

No adverse effects on male or female fertility or reproduction were observed in rats at doses producing plasma exposures (AUC) up to approximately 2 times the plasma AUC in humans at the MRHD.

14 CLINICAL STUDIES

The efficacy of MOTPOLY XR is based on the relative bioavailability of MOTPOLY XR compared to immediate release lacosamide in healthy adults [ see Clinical Pharmacology (12.3)] .

14.1 Monotherapy in Patients with Partial-Onset Seizures

The efficacy of immediate-release lacosamide in monotherapy was established in a historical-control, multicenter, randomized trial that included 425 patients, age 16 to 70 years, with partial-onset seizures (Study 1). To be included in Study 1, patients were required to be taking stable doses of 1 or 2 marketed antiepileptic drugs. This treatment continued into the 8-week baseline period. To remain in the study, patients were required to have at least 2 partial-onset seizures per 28 days during the 8-week baseline period. The baseline period was followed by a 3-week titration period, during which lacosamide was added to the ongoing antiepileptic regimen. This was followed by a 16-week maintenance period (i.e., a 6-week withdrawal period for background antiepileptic drugs, followed by a 10-week monotherapy period). Patients were randomized 3 to 1 to receive lacosamide 400 mg/day or lacosamide 300 mg/day. Treatment assignments were blinded. Response to treatment was based upon a comparison of the number of patients who met exit criteria during the maintenance phase, compared to historical controls. The historical control consisted of a pooled analysis of the control groups from 8 studies of similar design, which utilized a sub-therapeutic dose of an antiepileptic drug. Statistical superiority to the historical control was considered to be demonstrated if the upper limit from a 2-sided 95% confidence interval for the percentage of patients meeting exit criteria in patients receiving lacosamide remained below the lower 95% prediction limit of 65% derived from the historical control data.

The exit criteria were one or more of the following: (1) doubling of average monthly seizure frequency during any 28 consecutive days, (2) doubling of highest consecutive 2-day seizure frequency, (3) clinically significant prolongation or worsening of overall seizure duration, frequency, type or pattern considered by the investigator to require trial discontinuation, (4) status epilepticus or new onset of serial/cluster seizures. The study population profile appeared comparable to that of the historical control population.
For the lacosamide 400 mg/day group, the estimate of the percentage of patients meeting at least 1 exit criterion was 30% (95% CI: 25%, 36%). The upper limit of the 2-sided 95% CI (36%) was below the threshold of 65% derived from the historical control data, meeting the pre-specified criteria for efficacy. Lacosamide 300 mg/day also met the pre-specified criteria for efficacy.

14.2 Adjunctive Therapy in Patients with Partial-Onset Seizures

The efficacy of lacosamide as adjunctive therapy in partial-onset seizures was established in three 12-week, randomized, double-blind, placebo-controlled, multicenter trials in adult patients (Study 2, Study 3, and Study 4). Enrolled patients had partial-onset seizures with or without secondary generalization and were not adequately controlled with 1 to 3 concomitant AEDs. During an 8-week baseline period, patients were required to have an average of ≥4 partial-onset seizures per 28 days with no seizure-free period exceeding 21 days. In these 3 trials, patients had a mean duration of epilepsy of 24 years and a median baseline seizure frequency ranging from 10 to 17 per 28 days. 84% of patients were taking 2 to 3 concomitant AEDs with or without concurrent vagal nerve stimulation.

Study 2 compared doses of lacosamide 200, 400, and 600 mg/day with placebo. Study 3 compared doses of lacosamide 400 and 600 mg/day with placebo. Study 4 compared doses of lacosamide 200 and 400 mg/day with placebo. In all three trials, following an 8-week baseline phase to establish baseline seizure frequency prior to randomization, patients were randomized and titrated to the randomized dose (a 1-step back-titration of lacosamide 100 mg/day or placebo was allowed in the case of intolerable adverse events at the end of the titration phase). During the titration phase, in all 3 adjunctive therapy trials, treatment was initiated at 100 mg/day (50 mg twice daily), and increased in weekly increments of 100 mg/day to the target dose. The titration phase lasted 6 weeks in Study 2 and Study 3, and 4 weeks in Study 4. In all three trials, the titration phase was followed by a maintenance phase that lasted 12 weeks, during which patients were to remain on a stable dose of lacosamide.

A reduction in 28-day seizure frequency (baseline to maintenance phase), as compared to the placebo group, was the primary variable in all three adjunctive therapy trials. A statistically significant effect was observed with lacosamide treatment (Figure 1) at doses of 200 mg/day (Study 4), 400 mg/day (Studies 2, 3, and 4), and 600 mg/day (Studies 2 and 3).

Subset evaluations of lacosamide demonstrate no important differences in seizure control as a function of gender or race, although data on race was limited (about 10% of patients were non-Caucasian).

Figure 2 presents the percentage of patients (X-axis) with a percent reduction in partial seizure frequency (responder rate) from baseline to the maintenance phase at least as great as that represented on the Y-axis. A positive value on the Y-axis indicates an improvement from baseline (i.e., a decrease in seizure frequency), while a negative value indicates a worsening from baseline (i.e., an increase in seizure frequency). Thus, in a display of this type, a curve for an effective treatment is shifted to the left of the curve for placebo. The proportion of patients achieving any particular level of reduction in seizure frequency was consistently higher for the lacosamide groups, compared to the placebo group. For example, 40% of patients randomized to lacosamide (400 mg/day) experienced a 50% or greater reduction in seizure frequency, compared to 23% of patients randomized to placebo. Patients with an increase in seizure frequency >100% are represented on the Y-axis as equal to or greater than -100%.

14.3 Adjunctive Therapy in Patients with Primary Generalized Tonic-Clonic Seizures

The efficacy of immediate-release lacosamide as adjunctive therapy in patients weighing 50 kg or more with idiopathic generalized epilepsy experiencing primary generalized tonic-clonic (PGTC) seizures was established in a 24-week double-blind, randomized, placebo-controlled, parallel-group, multi-center study (Study 5). The study consisted of a 12-week historical baseline period, a 4-week prospective baseline period, and a 24-week treatment period (which included a 6-week titration period and an 18-week maintenance period). Eligible patients on a stable dose of 1 to 3 antiepileptic drugs experiencing at least 3 documented PGTC seizures during the 16-week combined baseline period were randomized 1:1 to receive lacosamide or placebo. Patients were dosed on a fixed-dose regimen. Dosing was initiated at a dose of 100 mg/day in patients weighing 50 kg or more in 2 divided doses. During the titration period, lacosamide doses were adjusted in 100 mg/day increments at weekly intervals to achieve the target maintenance period dose of 400 mg/day in patients weighing 50 kg or more, which was one of three weight-based dosing arms. The primary efficacy endpoint was the time to second PGTC seizure during the 24-week treatment period (Figure 3). The risk of developing a second PGTC seizure was statistically significantly lower in the lacosamide group than in the placebo group during the 24-week treatment period (hazard ratio=0.548, 95% CI of hazard ratio: 0.381, 0.788, p-value = 0.001), with the corresponding risk reduction being 45.2%.

The key secondary efficacy endpoint was the percentage of patients not experiencing a PGTC seizure during the 24-week treatment period. The adjusted Kaplan-Meier estimates of 24-week freedom from PGTC seizures were 31.3% in lacosamide group and 17.2% in placebo group. The adjusted difference between treatment groups was 14.1% (95% CI: 3.2, 25.1, p-value=0.011).

Additional pediatric use information is approved for UCB Inc.'s Vimpat (lacosamide) tablets, oral solution, and intravenous solution. However, due to UCB Inc.'s marketing exclusivity rights, this drug product is not labeled with that pediatric information.

16 HOW SUPPLIED/STORAGE AND HANDLING

16.1 How Supplied

MOTPOLY XR extended-release capsules contain white or off-white beads and are available in the following strengths:

- 100 mg are yellow opaque cap with “A” printed in black ink and a white opaque body with “100” printed in black ink. They are supplied as follows:

Bottles of 60 NDC 73289-0063-2

- 150 mg are brown opaque cap with “A” printed in black ink and a white opaque body with “150” printed in black ink. They are supplied as follows:

Bottles of 60 NDC 73289-0064-2

- 200 mg are blue opaque cap with “A” printed in black ink and a white opaque body with “200” printed in black ink. They are supplied as follows:

Bottles of 60 NDC 73289-0065-2

16.2 Storage and Handling

Store at 20°C to 25°C (68°F to 77°F); excursions permitted between 15°C to 30°C (59°F to 86°F).

[See USP Controlled Room Temperature]

17 PATIENT COUNSELING INFORMATION

Advise the patient or caregiver to read the FDA-approved patient labeling (Medication Guide).

Administration

Inform patients that MOTPOLY XR should be swallowed whole with liquid. Instruct patients to not open, chew, or crush the capsules [ see Dosage and Administration (2.5)] .

Suicidal Thinking and Behavior

Patients, their caregivers, and families should be counseled that AEDs, including MOTPOLY XR, may increase the risk of suicidal thoughts and behavior and should be advised of the need to be alert for the emergence or worsening of symptoms of depression, any unusual changes in mood or behavior, or the emergence of suicidal thoughts, behavior, or thoughts about self-harm. Behaviors of concern should be reported immediately to healthcare providers [ see Warnings and Precautions (5.1)] .

Dizziness and Ataxia

Patients should be counseled that MOTPOLY XR use may cause dizziness, double vision, abnormal coordination and balance, and somnolence. Patients taking MOTPOLY XR should be advised not to drive, operate complex machinery, or engage in other hazardous activities until they have become accustomed to any such effects associated with MOTPOLY XR [ see Warnings and Precautions (5.2)] .

Cardiac Rhythm and Conduction Abnormalities

Patients should be counseled that MOTPOLY XR is associated with electrocardiographic changes that may predispose to irregular heart beat and syncope. Cardiac arrest has been reported. This risk is increased in patients with underlying cardiovascular disease, with heart conduction problems, or who are taking other medications that affect the heart. Patients should be made aware of and report cardiac signs or symptoms to their healthcare provider right away. Patients who develop syncope should lay down with raised legs and contact their health care provider [ see Warnings and Precautions (5.3)] .

Drug Reaction with Eosinophilia and Systemic Symptoms (DRESS)/Multi-Organ Hypersensitivity

Patients should be aware that MOTPOLY XR may cause serious hypersensitivity reactions affecting multiple organs such as the liver and kidney. MOTPOLY XR should be discontinued if a serious hypersensitivity reaction is suspected. Patients should also be instructed to report promptly to their physicians any symptoms of liver toxicity (e.g., fatigue, jaundice, dark urine) [ see Warnings and Precautions (5.6)] .

Pregnancy Registry

Advise patients to notify their healthcare provider if they become pregnant or intend to become pregnant during MOTPOLY XR therapy. Encourage patients to enroll in the North American Antiepileptic Drug (NAAED) pregnancy registry if they become pregnant. This registry is collecting information about the safety of AEDs during pregnancy [ see Use in Specific Populations (8.1)].

Lactation
Advise breastfeeding women using MOTPOLY XR to monitor infants for excess sleepiness and to seek medical care if they notice this sign [ see Use in Specific Populations (8.2) ].

Manufactured for: Aucta Pharmaceuticals, Inc. Piscataway, NJ 08854

LB5040-01

MEDICATION GUIDE
MOTPOLY XR (mot paa'lee)

lacosamide
extended release capsules, for

oral use, CV

Read this Medication Guide before you start taking MOTPOLY XR and each time you get a refill. There may be new information. This Medication Guide describes important safety information about MOTPOLY XR. This information does not take the place of talking to your healthcare provider about your medical condition or treatment.

What is the most important information I should know about MOTPOLY XR?
Do not stop taking MOTPOLY XR without first talking to your healthcare provider. Stopping MOTPOLY XR suddenly can cause serious problems. Stopping seizure medicine suddenly in a patient who has epilepsy can cause seizures that will not stop (status epilepticus).
MOTPOLY XR can cause serious side effects, including:

1. Like other antiepileptic drugs, MOTPOLY XR may cause suicidal thoughts or actions in a very small number of people, about 1 in 500.
Call a healthcare provider right away if you have any of these symptoms, especially if they are new, worse, or worry you :

- thoughts about suicide or dying
- attempt to commit suicide
- new or worse depression
- new or worse anxiety
- feeling agitated or restless
- panic attacks

- trouble sleeping (insomnia)
- new or worse irritability
- acting aggressive, being angry, or violent
- acting on dangerous impulses
- an extreme increase in activity and talking (mania)
- other unusual changes in behavior or mood

How can I watch for early symptoms of suicidal thoughts and actions?

- Pay attention to any changes, especially sudden changes, in mood, behaviors, thoughts, or feelings.
- Keep all follow-up visits with your healthcare provider as scheduled.
- Call your healthcare provider between visits as needed, especially if you are worried about symptoms.
- Suicidal thoughts or actions can be caused by things other than medicines. If you have suicidal thoughts or actions, your healthcare provider may check for other causes.

2.MOTPOLY XR may cause you to feel dizzy, have double vision, feel sleepy, or have problems with coordination and walking. Do not drive, operate heavy machinery, or do other dangerous activities until you know how MOTPOLY XR affects you.

3.MOTPOLY XR may cause you to have an irregular heartbeat or may cause you to faint. In rare cases, cardiac arrest has been reported. Call your healthcare provider right away if you:

- have a fast, slow, or pounding heartbeat or feel your heart skip a beat
- have shortness of breath
- have chest pain

- feel lightheaded
- fainted or if you feel like you are going to faint

If you have fainted or feel like you are going to faint you should lay down with your legs raised.

4.MOTPOLY XR is a federally controlled substance (CV) because it can be abused or lead to drug dependence. Keep your MOTPOLY XR in a safe place, to protect it from theft. Never give your MOTPOLY XR to anyone else, because it may harm them. Selling or giving away this medicine is against the law.

What is MOTPOLY XR?

MOTPOLY XRis a prescription medicine used:

- to treat partial-onset seizures in adults and in children weighing at least 110 pounds (50 kg).
- with other medicines to treat primary generalized tonic-clonic seizures in adults and children weighing at least 110 pounds (50 kg).

It is not known if MOTPOLY XR is safe and effective for partial-onset seizures and primary generalized tonic-clonic seizuresin children weighing less than 50 kg.

What should I tell my healthcare provider before taking MOTPOLY XR?
Before you take MOTPOLY XR, tell your healthcare provider about all of your medical conditions, including if you :

- have or have had depression, mood problems or suicidal thoughts or behavior.
- have heart problems.
- have kidney problems.
- have liver problems.
- have abused prescription medicines, street drugs or alcohol in the past.
- are pregnant or plan to become pregnant. It is not known if MOTPOLY XR can harm your unborn baby. Tell your healthcare provider right away if you become pregnant while taking MOTPOLY XR. You and your healthcare provider will decide if you should take MOTPOLY XR while you are pregnant.
  - If you become pregnant while taking MOTPOLY XR, talk to your healthcare provider about registering with the North American Antiepileptic Drug Pregnancy Registry. You can enroll in this registry by calling 1-888-233-2334. The purpose of this registry is to collect information about the safety of antiepileptic medicine during pregnancy.
- are breastfeeding or plan to breastfeed. MOTPOLY XR passes into your breast milk.
- Breastfeeding during treatment with MOTPOLY XR may cause your baby to have more sleepiness than normal. If this happens, contact your baby’s healthcare provider.
- Talk to your healthcare provider about the best way to feed your baby if you take MOTPOLY XR.

Tell your healthcare provider about all the medicines you take, including prescription and over-the-counter medicines, vitamins, and herbal supplements.
Taking MOTPOLY XR with certain other medicines may cause side effects or affect how well they work. Do not start or stop other medicines without talking to your healthcare provider. Know the medicines you take. Keep a list of them and show it to your healthcare provider and pharmacist each time you get a new medicine.

How should I take MOTPOLY XR?

- Take MOTPOLY XR exactly as your healthcare provider tells you.

- Your healthcare provider will tell you how much MOTPOLY XR to take and when to take it.
- Your healthcare provider may change your dose if needed.
- Do not stop MOTPOLY XR without first talking to a healthcare provider. Stopping MOTPOLY XR suddenly in a patient who has epilepsy can cause seizures that will not stop (status epilepticus).
- MOTPOLY XR may be taken with or without food.
- Swallow MOTPOLY XR whole with liquid. Do not open, chew, or crush the capsules.

- If you take too much MOTPOLY XR, call your healthcare provider or local Poison Control Center right away.

What should I avoid while taking MOTPOLY XR?

- Do not drive, operate heavy machinery, or do other dangerous activities until you know how MOTPOLY XR affects you.
- MOTPOLY XR may cause you to feel dizzy, have double vision, feel sleepy, or have problems with coordination and walking.
- You should not drink alcohol while taking MOTPOLY XR. MOTPOLY XR and alcohol can affect each other causing side effects such as sleepiness and dizziness.

What are the possible side effects of MOTPOLY XR?

- See " What is the most important information I should know about MOTPOLY XR?"

MOTPOLY XR may cause other serious side effects including:

- A serious allergic reaction that may affect your skin or other parts of your body such as your liver or blood cells. Call your healthcare provider right away if you have:

- a skin rash, hives
- fever or swollen glands that do not go away
- shortness of breath
- tiredness (fatigue)

- swelling of the legs
- yellowing of the skin or whites of the eyes
- dark urine

The most common side effects of MOTPOLY XR include:

- double vision
- headache
- dizziness

- nausea
- sleepiness

These are not all of the possible side effects of MOTPOLY XR. For more information ask your healthcare provider or pharmacist. Tell your healthcare provider about any side effect that bothers you or that does not go away. Call your doctor for medical advice about side effects. You may report side effects to FDA at 1-800-FDA-1088.

How should I store MOTPOLY XR?

- Store MOTPOLY XR at room temperature between 68ºF to 77ºF (20ºC to 25ºC).

Keep MOTPOLY XR and all medicines out of the reach of children.

General Information about the safe and effective use of MOTPOLY XR.
Medicines are sometimes prescribed for purposes other than those listed in a Medication Guide. Do not use MOTPOLY XR for a condition for which it was not prescribed. Do not give MOTPOLY XR to other people, even if they have the same symptoms that you have. It may harm them.
You can ask your pharmacist or healthcare provider for information about MOTPOLY XR that is written for health professionals.

What are the ingredients in MOTPOLY XR?
Active ingredient : lacosamide
Capsule inactive ingredients:ethylcellulose, hypromellose, microcrystalline cellulose, povidone, titanium dioxide, triacetin, triethyl citrate, and additional ingredients listed below:

- 100 mg capsules: red iron oxide
- 150 mg capsules: red iron oxide, yellow iron oxide
- 200 mg capsules: black iron oxide, FD&C Blue #1, red iron oxide

Manufactured for: Aucta Pharmaceuticals, Inc. Piscataway NJ 08854

This Medication Guide has been approved by the U.S. Food and Drug Administration

Revised: 6/2024

PRINCIPAL DISPLAY PANEL - 100 mg Capsule Bottle Label

NDC 73289-0063-2

Motpoly XR (lacosamide) extended-release capsules
CV

100 mg

Rx only 60 Capsules

ATTENTION PHARMACIST:
Each patient is required to receive
the accompanying Medication Guide

Each capsule contains
100 mg lacosamide.

Keep this and all drugs
out of reach of children.

Recommended Dosage:
See prescribing Information.

Swallow capsules whole
with liquid. Do not open,
chew or crush.

Manufactured for:
Aucta Pharmoceutlcals, Inc.
Piscataway, NJ 08854

Store at 20˚ C to 25˚ C (68˚ F to 77˚ F);
excursions permitted between 15˚ C to
30˚ C (59˚ F to 86˚ F).
[See USP Controlled Room Temperature]

PRINCIPAL DISPLAY PANEL - 150 mg Capsule Bottle Label

NDC 73289-0064-2

Motpoly XR (lacosamide) extended-release capsules
CV

150 mg

Rx only
60 Capsules

ATTENTION PHARMACIST:
Each patient is required to receive the
accompanying Medication Guide.

Each capsule contains
150 mg lacosamide.

Keep this and all drugs
out of reach of children.

Recommended Dosage:
See prescribing information.

Swallow capsules whole
with liquid. Do not open,
chew or crush.

Manufactured for:
Aucta Pharmaceuticals, Inc.
Piscataway, NJ 08854

Store at 20˚ C to 25˚ C (68˚ F to 77˚ F);
excursions permitted between 15˚ C to
30˚ C (59˚ F to 86˚ F).
[See USP Controlled Room Temperature]

PRINCIPAL DISPLAY PANEL - 200 mg Capsule Bottle Label

NDC 73289-0065-2

Motpoly XR (lacosamide) extended-release capsules
CV

200 mg

Rx only
60 Capsules

ATTENTION PHARMACIST:
Each patient is required to receive the
accompanying Medication Guide.

Each capsule contains
200 mg lacosamide.

Keep this and all drugs
out of reach of children.

Recommended Dosage:
See prescribing information.

Swallow capsules whole
with liquid. Do not open,
chew or crush.

Manufactured for:
Aucta Pharmaceuticals, Inc.
Piscataway, NJ 08854

Store at 20˚ C to 25˚ C (68˚ F to 77˚ F);
excursions permitted between 15˚ C to
30˚ C (59˚ F to 86˚ F).
[See USP Controlled Room Temperature]

PRINCIPAL DISPLAY PANEL - Physician Samples

Professional Sample – Not for Sale

NDC 73289-0063-1

Motpoly XR (lacosamide) extended-release capsules

CV

100 mg per capsule

ATTENTION PHYSICIAN:
Each patient is required to receive
the accompanying Medication Guide.

Rx Only 14 Capsules

Each capsule contains 100 mg lacosamide.
Recommended Dosage: See prescribing information.
Swallow capsules whole with liquid. Do not open, chew or crush.
Store at 20°C to 25°C (68°F to 77°F); excursions permitted between
15°C to 30°C (59°F to 86°F). [See USP Controlled Room Temperature].

Manufactured for:

Aucta Pharmaceuticals, Inc.

Piscataway, NJ 08854